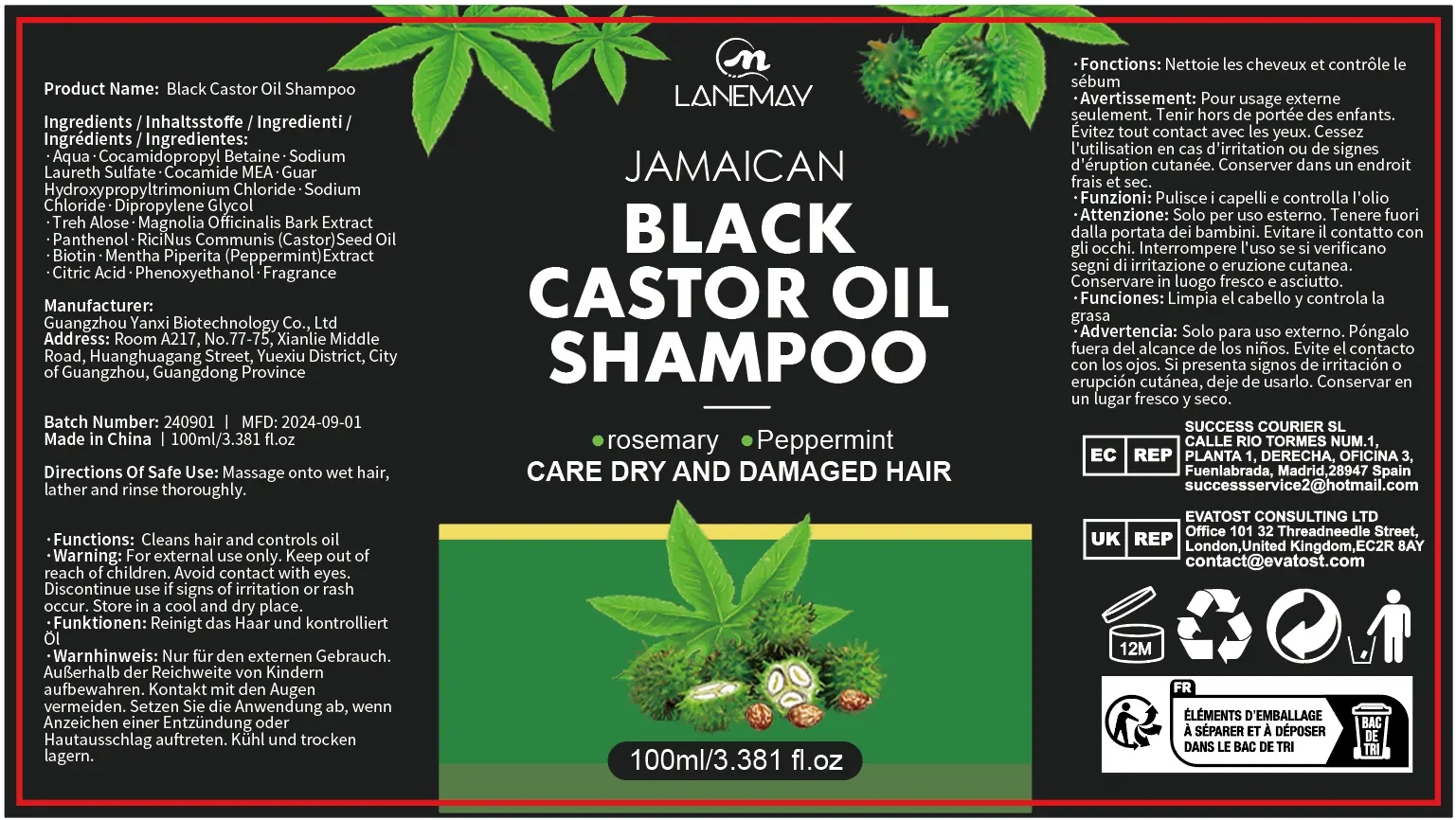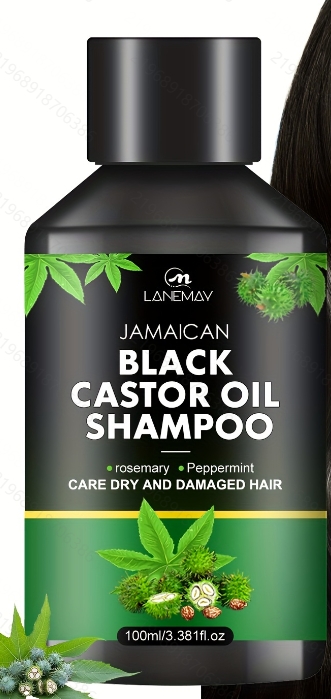 DRUG LABEL: Black Castor OilShampoo
NDC: 84025-209 | Form: SHAMPOO
Manufacturer: Guangzhou Yanxi Biotechnology Co., Ltd
Category: otc | Type: HUMAN OTC DRUG LABEL
Date: 20241012

ACTIVE INGREDIENTS: COCAMIDOPROPYL BETAINE 5 mg/100 mL; DIPROPYLENE GLYCOL 3 mg/100 mL
INACTIVE INGREDIENTS: WATER

DOSAGE AND ADMINISTRATION

ues as a normal hair cream

WARNINGS

keep out of children

INACTIVE INGREDIENT

Aqua

INDICATIONS AND USAGE

for daily hair care

keep out of children

PURPOSE

strong and nourishing hair